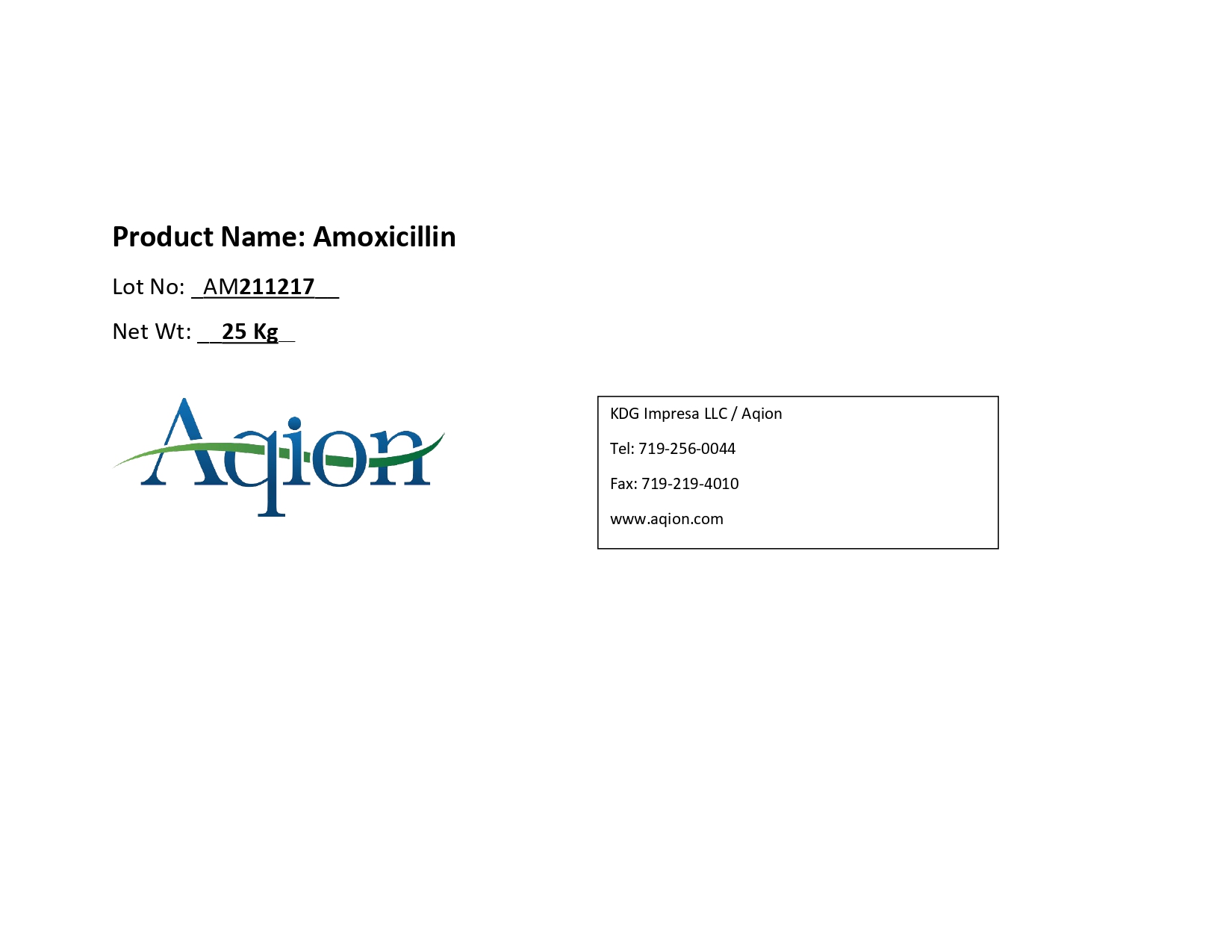 DRUG LABEL: Amoxicillin
NDC: 43457-539 | Form: POWDER
Manufacturer: KDG Impresa LLC, Aqion
Category: other | Type: BULK INGREDIENT - ANIMAL DRUG
Date: 20220222

ACTIVE INGREDIENTS: AMOXICILLIN 1 kg/1 kg

Amoxicillin